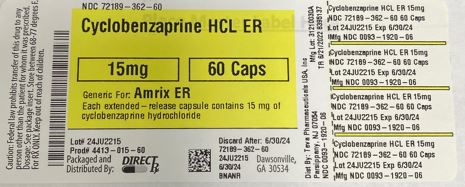 DRUG LABEL: Cyclobenzaprine HCL ER
NDC: 72189-362 | Form: CAPSULE, EXTENDED RELEASE
Manufacturer: Direct_Rx
Category: prescription | Type: HUMAN PRESCRIPTION DRUG LABEL
Date: 20250122

ACTIVE INGREDIENTS: CYCLOBENZAPRINE HYDROCHLORIDE 15 mg/1 1
INACTIVE INGREDIENTS: POLYETHYLENE GLYCOL 8000; SUCROSE; TITANIUM DIOXIDE; FD&C BLUE NO. 1; STARCH, CORN; FD&C RED NO. 40; FD&C BLUE NO. 2; DIETHYL PHTHALATE; ETHYLCELLULOSE (10 MPA.S); HYPROMELLOSE 2910 (6 MPA.S); POLYETHYLENE GLYCOL 400; FD&C YELLOW NO. 6; GELATIN, UNSPECIFIED

Cyclobenzaprine HCL ER

INDICATIONS AND USAGE

Cyclobenzaprine hydrochloride extended-release capsules are indicated as an adjunct to rest and physical therapy for relief of muscle spasm associated with acute, painful musculoskeletal conditions. Improvement is manifested by relief of muscle spasm and its associated signs and symptoms, namely, pain, tenderness, and limitation of motion.

Limitations of Use:

Cyclobenzaprine hydrochloride extended-release capsules should be used only for short periods (up to two or three weeks) because adequate evidence of effectiveness for more prolonged use is not available and because muscle spasm associated with acute, painful musculoskeletal conditions is generally of short duration and specific therapy for longer periods is seldom warranted.
Cyclobenzaprine hydrochloride extended-release capsules have not been found effective in the treatment of spasticity associated with cerebral or spinal cord disease or in children with cerebral palsy.

DOSAGE AND ADMINISTRATION

The recommended adult dose for most patients is one (1) cyclobenzaprine hydrochloride extended-release 15 mg capsule taken once daily. Some patients may require up to 30 mg/day, given as one (1) cyclobenzaprine hydrochloride extended-release 30 mg capsule taken once daily or as two (2) cyclobenzaprine hydrochloride extended-release 15 mg capsules taken once daily.

It is recommended that doses be taken at approximately the same time each day.
Use of cyclobenzaprine hydrochloride extended-release capsules for periods longer than two or three weeks is not recommended [SEE INDICATIONS AND USAGE (1)].

Instruct patients to swallow cyclobenzaprine hydrochloride extended-release capsules intact. Alternatively, the contents of the cyclobenzaprine hydrochloride extended-release capsule may be sprinkled over applesauce and then swallowed. This method is appropriate only for patients able to reliably swallow the applesauce without chewing. Other foods have not been tested and should not be substituted for applesauce. Instruct the patient to:

Sprinkle the contents of the capsule onto a tablespoon of applesauce and consume immediately without chewing.
Rinse the mouth to ensure all of the contents have been swallowed.
Discard any unused portion of the cyclobenzaprine hydrochloride extended-release capsules after the contents have been sprinkled on applesauce.

Extended-release capsules in the following strengths:

15 mg: Capsules are orange/orange and are embossed in blue ink with “15 mg” on the body, and Cephalon “C” logo, “Cephalon,” and a dashed band on the cap.
30 mg: Capsules are blue/red and are embossed in white ink with “30 mg” on the body, and Cephalon “C” logo, “Cephalon,” and a dashed band on the cap.

CONTRAINDICATIONS

Hypersensitivity to any component of this product. These adverse reactions may manifest as an anaphylactic reaction, urticaria, facial and/or tongue swelling, or pruritus. Discontinue cyclobenzaprine hydrochloride extended-release capsules if a hypersensitivity reaction is suspected.
Concomitant use of monoamine oxidase (MAO) inhibitors or within 14 days after their discontinuation. Hyperpyretic crisis seizures and deaths have occurred in patients receiving cyclobenzaprine (or structurally similar tricyclic antidepressants) concomitantly with MAO inhibitor drugs.
During the acute recovery phase of myocardial infarction, and in patients with arrhythmias, heart block or conduction disturbances, or congestive heart failure.
Hyperthyroidism.

WARNINGS AND PRECAUTIONS

5.1 Serotonin Syndrome

The development of a potentially life-threatening serotonin syndrome has been reported with cyclobenzaprine when used in combination with other drugs, such as selective serotonin reuptake inhibitors (SSRIs), serotonin norepinephrine reuptake inhibitors (SNRIs), tricyclic antidepressants (TCAs), tramadol, bupropion, meperidine, verapamil, or MAO inhibitors. The concomitant use of cyclobenzaprine hydrochloride extended-release capsules with MAO inhibitors is contraindicated [SEE CONTRAINDICATIONS (4)]. Serotonin syndrome symptoms may include mental status changes (e.g., confusion, agitation, hallucinations), autonomic instability (e.g., diaphoresis, tachycardia, labile blood pressure, hyperthermia), neuromuscular abnormalities (e.g., tremor, ataxia, hyperreflexia, clonus, muscle rigidity), and/or gastrointestinal symptoms (e.g., nausea, vomiting, diarrhea). Treatment with cyclobenzaprine hydrochloride extended-release capsules and any concomitant serotonergic agents should be discontinued immediately if the above reactions occur and supportive symptomatic treatment should be initiated. If concomitant treatment with cyclobenzaprine hydrochloride extended-release capsules and other serotonergic drugs is clinically warranted, careful observation is advised, particularly during treatment initiation or dose increases.

5.2 Tricyclic Antidepressant-like Effects

Cyclobenzaprine is structurally related to the tricyclic antidepressants, e.g., amitriptyline and imipramine. Tricyclic antidepressants have been reported to produce arrhythmias, sinus tachycardia, prolongation of the conduction time leading to myocardial infarction and stroke [SEE CONTRAINDICATIONS (4)]. Cyclobenzaprine hydrochloride extended-release capsules may enhance the effects of alcohol, barbiturates, and other CNS depressants.

Some of the more serious central nervous system (CNS) reactions noted with the tricyclic antidepressants have occurred in short-term studies of cyclobenzaprine for indications other than muscle spasm associated with acute musculoskeletal conditions, and usually at doses somewhat greater than those recommended for skeletal muscle spasm. If clinically significant CNS symptoms develop, consider discontinuation of cyclobenzaprine hydrochloride extended-release capsules.

5.3 Use in the Elderly

As a result of a 40% increase in cyclobenzaprine plasma levels and a 56% increase in plasma half-life following administration of cyclobenzaprine hydrochloride extended-release capsules in elderly subjects as compared to young adults, use of cyclobenzaprine hydrochloride extended-release capsules is not recommended in the elderly [SEE CLINICAL PHARMACOLOGY (12.3)].

5.4 Use in Patients with Hepatic Impairment

As a result of two-fold higher cyclobenzaprine plasma levels in subjects with mild hepatic impairment, as compared to healthy subjects, following administration of immediate-release cyclobenzaprine and because there is limited dosing flexibility with cyclobenzaprine hydrochloride extended-release capsules, use of cyclobenzaprine hydrochloride extended-release capsules is not recommended in patients with mild, moderate, or severe hepatic impairment [SEE CLINICAL PHARMACOLOGY (12.3)].

5.5 Atropine-like Action

Because of its atropine-like action, cyclobenzaprine hydrochloride extended-release capsules should be used with caution in patients with a history of urinary retention, angle-closure glaucoma, increased intraocular pressure, and in patients taking anticholinergic medication.

ADVERSE REACTIONS

The following clinically significant reactions are described in greater detail, in other sections.

Serotonin Syndrome [see Warnings and Precautions (5.1)]

Adverse Cardiovascular Effects [see Warnings and Precautions (5.2)]

6.1 Clinical Trials Experience

Because clinical trials are conducted under widely varying conditions, adverse reaction rates observed in the clinical trials of a drug cannot be directly compared to rates in the clinical trials of another drug and may not reflect the rates observed in clinical practice.

The data described below reflect exposure to cyclobenzaprine hydrochloride extended-release capsules in 253 patients in 2 clinical trials. Cyclobenzaprine hydrochloride extended-release capsules were studied in two double-blind, parallel-group, placebo-controlled, active-controlled trials of identical design [SEE CLINICAL STUDIES (14)]. The study population was composed of patients with muscle spasms associated with acute painful musculoskeletal conditions. Patients received 15 mg or 30 mg of cyclobenzaprine hydrochloride extended-release capsules taken orally once daily, cyclobenzaprine immediate-release (IR) 10 mg three times a day, or placebo for 14 days.

The most common adverse reactions (incidence ≥3% in any treatment group and greater than placebo) were dry mouth, dizziness, fatigue, constipation, nausea, dyspepsia, and somnolence (see Table 1).

Table 1: Incidence of the Most Common Adverse Reactions Occurring in ≥ 3% of Patients in any Treatment Group* and Greater Than Placebo in the Two Phase 3, Double-Blind Cyclobenzaprine Hydrochloride Extended-Release Capsules Trials

Placebo

Cyclobenzaprine Hydrochloride Extended-Release Capsules 15 mg

Cyclobenzaprine Hydrochloride Extended-Release Capsules 30 mg

N=128

N=127

N=126

Dry mouth

2%

6%

14%

Dizziness

2%

3%

6%

Fatigue

2%

3%

3%

Constipation

0%

1%

3%

Somnolence

0%

1%

2%

Nausea

1%

3%

3%

Dyspepsia

1%

0%

4%

*cyclobenzaprine hydrochloride extended-release capsules 15 mg QD, cyclobenzaprine hydrochloride extended-release capsules 30 mg QD, or cyclobenzaprine IR tablets TID

6.2 Postmarketing Experience

The following adverse reactions have been reported in clinical studies or postmarketing experience with cyclobenzaprine hydrochloride extended-release capsules, cyclobenzaprine IR, or tricyclic drugs. Because some of these reactions are reported voluntarily from a population of uncertain size, it is not always possible to reliably estimate their frequency or establish a causal relationship to drug exposure.

In a postmarketing surveillance program of cyclobenzaprine IR, the adverse reactions reported most frequently were drowsiness, dry mouth, and dizziness and adverse reactions reported in 1% to 3% of the patients were: fatigue/tiredness, asthenia, nausea, constipation, dyspepsia, unpleasant taste, blurred vision, headache, nervousness, and confusion.

The following adverse reactions have been reported in postmarketing experience (cyclobenzaprine hydrochloride extended-release capsules or cyclobenzaprine IR), in clinical studies of cyclobenzaprine IR (incidence <1%), or in postmarketing experience with other tricyclic drugs:

Body as a Whole: Syncope; malaise; chest pain; edema.

Cardiovascular: Tachycardia; arrhythmia; vasodilatation; palpitation; hypotension; hypertension; myocardial infarction; heart block; stroke.

Digestive: Vomiting; anorexia; diarrhea; gastrointestinal pain; gastritis; thirst; flatulence; edema of the tongue; abnormal liver function and rare reports of hepatitis, jaundice, and cholestasis; paralytic ileus, tongue discoloration; stomatitis; parotid swelling.

Endocrine: Inappropriate ADH syndrome.

Hematologic and Lymphatic: Purpura; bone marrow depression; leukopenia; eosinophilia; thrombocytopenia.

Hypersensitivity: Anaphylaxis; angioedema; pruritus; facial edema; urticaria; rash.

Metabolic, Nutritional, and Immune: Elevation and lowering of blood sugar levels; weight gain or loss.

Musculoskeletal: Local weakness; myalgia.

Nervous System and Psychiatric: Seizures; ataxia; vertigo; dysarthria; tremors; hypertonia; convulsions; muscle twitching; disorientation; insomnia; depressed mood; abnormal sensations; anxiety; agitation; psychosis; abnormal thinking and dreaming; hallucinations; excitement; paresthesia; diplopia; serotonin syndrome; neuroleptic malignant syndrome; decreased or increased libido; abnormal gait; delusions; aggressive behavior; paranoia; peripheral neuropathy; Bell’s palsy; alteration in EEG patterns; extrapyramidal symptoms.

Respiratory: Dyspnea.

Skin: Sweating; photosensitization; alopecia.

Special Senses: Ageusia; tinnitus.

Urogenital: Urinary frequency and/or retention; impaired urination; dilatation of urinary tract; impotence; testicular swelling; gynecomastia; breast enlargement; galactorrhea.

DRUG INTERACTIONS

Based on its structural similarity to tricyclic antidepressants, cyclobenzaprine hydrochloride extended-release capsules may have life-threatening interactions with MAO inhibitors [SEE CONTRAINDICATIONS (4)], may enhance the effects of alcohol, barbiturates, and other CNS depressants, may enhance the seizure risk in patients taking tramadol, or may block the antihypertensive action of guanethidine and similarly acting compounds.

Postmarketing cases of serotonin syndrome have been reported during combined use of cyclobenzaprine and other drugs, such as SSRIs, SNRIs, TCAs, tramadol, bupropion, meperidine, verapamil, or MAO inhibitors [SEE WARNINGS AND PRECAUTIONS (5.1)].

USE IN SPECIFIC POPULATIONS

8.1 Pregnancy

Risk Summary

Available data from case reports with cyclobenzaprine hydrochloride extended-release capsules use in pregnancy have not identified a drug-associated risk of major birth defects, miscarriage, or adverse maternal or fetal outcomes. In rats, decreased pup body weight and survival was noted at cyclobenzaprine doses ≥10 mg/kg/day (approximately ≥3 times the maximum recommended human dose (MRHD) of 30 mg/day), when administered orally during pregnancy and lactation (see Data).

The estimated background risk of major birth defects and miscarriage for the indicated populations is unknown. All pregnancies have a background risk of birth defect, loss or other adverse outcomes. In the US general population, the estimated background risk of major birth defects and miscarriage in clinically recognized pregnancies is 2% to 4% and 15% to 20%, respectively.

Data

Animal Data

No adverse embryofetal effects were reported following oral administration of cyclobenzaprine during organogenesis to mice and rabbits at maternal doses up to 20 mg/kg/day (approximately 3 and 15 times the MRHD, respectively, on a mg/m2 basis). Maternal toxicity characterized by decreased body weight gain was observed only in mice at the highest tested dose of 20 mg/kg/day.

Decreased pup body weight and survival were reported in a prenatal and postnatal study where pregnant rats were treated orally with cyclobenzaprine during pregnancy and lactation with maternal doses of 10 and 20 mg/kg/day (approximately 3 and 6 times the MRHD on a mg/m2 basis). Maternal toxicity, characterized by a decreased body weight gain, was observed only at the highest tested dose of 20 mg/kg/day.

8.2 Lactation

Risk Summary

There are no data on the presence of cyclobenzaprine in either human or animal milk, the effects on a breastfed infant, or the effects on milk production. The developmental and health benefits of breastfeeding should be considered along with the mother’s clinical need for cyclobenzaprine hydrochloride extended-release capsules and any potential adverse effects on the breastfed child from cyclobenzaprine hydrochloride extended-release capsules or from the underlying maternal condition.

8.4 Pediatric Use

Safety and effectiveness of cyclobenzaprine hydrochloride extended-release capsules have not been studied in pediatric patients.

8.5 Geriatric Use

Clinical studies of cyclobenzaprine hydrochloride extended-release capsules did not include sufficient numbers of patients aged 65 and over to determine the safety and efficacy of cyclobenzaprine hydrochloride extended-release capsules in the elderly population. The plasma concentration and half-life of cyclobenzaprine are substantially increased in the elderly when compared to the general patient population. Accordingly, use of cyclobenzaprine hydrochloride extended-release capsules is not recommended in the elderly [SEE WARNINGS AND PRECAUTIONS (5.3) AND CLINICAL PHARMACOLOGY (12.3)].

8.6 Hepatic Impairment

The use of cyclobenzaprine hydrochloride extended-release capsules is not recommended in patients with mild, moderate, or severe hepatic impairment [SEE WARNINGS AND PRECAUTIONS (5.4) and CLINICAL PHARMACOLOGY (12.3)].

9.3 Dependence

Pharmacologic similarities among the tricyclic drugs require that certain withdrawal symptoms be considered when cyclobenzaprine hydrochloride extended-release capsules are administered, even though they have not been reported to occur with this drug. Abrupt cessation of treatment after prolonged administration rarely may produce nausea, headache, and malaise. These are not indicative of addiction.

OVERDOSAGE

10.1 Manifestations

Although rare, deaths may occur from overdosage with cyclobenzaprine hydrochloride extended-release capsules. Multiple drug ingestion (including alcohol) is common in deliberate cyclobenzaprine overdose. As management of overdose is complex and changing, it is recommended that the physician contact a poison control center for current information on treatment. Signs and symptoms of toxicity may develop rapidly after cyclobenzaprine overdose; therefore, hospital monitoring is required as soon as possible.

The most common effects associated with cyclobenzaprine overdose are drowsiness and tachycardia. Less frequent manifestations include tremor, agitation, coma, ataxia, hypertension, slurred speech, confusion, dizziness, nausea, vomiting, and hallucinations. Rare but potentially critical manifestations of overdose are cardiac arrest, chest pain, cardiac dysrhythmias, severe hypotension, seizures, and neuroleptic malignant syndrome. Changes in the electrocardiogram, particularly in QRS axis or width, are clinically significant indicators of cyclobenzaprine toxicity. Other potential effects of overdosage include any of the symptoms listed under ADVERSE REACTIONS (6).

10.2 Management

General

As management of overdose is complex and changing, it is recommended that the physician contact a poison control center for current information on treatment.

In order to protect against the rare but potentially critical manifestations described above, obtain an ECG and immediately initiate cardiac monitoring. Protect the patient’s airway, establish an intravenous line, and initiate gastric decontamination. Observation with cardiac monitoring and observation for signs of CNS or respiratory depression, hypotension, cardiac dysrhythmias and/or conduction blocks, and seizures is necessary. If signs of toxicity occur at any time during this period, extended monitoring is required. Monitoring of plasma drug levels should not guide management of the patient. Dialysis is probably of no value because of low plasma concentrations of the drug.

Gastrointestinal Decontamination

All patients suspected of an overdose with cyclobenzaprine hydrochloride extended-release capsules should receive gastrointestinal decontamination. This should include large volume gastric lavage followed by activated charcoal. If consciousness is impaired, the airway should be secured prior to lavage and emesis is contraindicated.

Cardiovascular

A maximal limb-lead QRS duration of 0.10 seconds may be the best indication of the severity of the overdose. Serum alkalinization, to a pH of 7.45 to 7.55, using intravenous sodium bicarbonate and hyperventilation (as needed), should be instituted for patients with dysrhythmias and/or QRS widening. A pH >7.60 or a pCO2 <20 mmHg is undesirable. Dysrhythmias unresponsive to sodium bicarbonate therapy/hyperventilation may respond to lidocaine, bretylium, or phenytoin. Type 1A and 1C antiarrhythmics are generally contraindicated (e.g., quinidine, disopyramide, and procainamide).

CNS

In patients with CNS depression, early intubation is advised because of the potential for abrupt deterioration. Seizures should be controlled with benzodiazepines or, if these are ineffective, other anticonvulsants (e.g., phenobarbital, phenytoin). Physostigmine is not recommended except to treat life-threatening symptoms that have been unresponsive to other therapies, and then only in close consultation with a poison control center.

Psychiatric Follow-Up

Since overdosage is often deliberate, patients may attempt suicide by other means during the recovery phase. Psychiatric referral may be appropriate.

Pediatric Management

The principles of management of child and adult overdosage are similar. It is strongly recommended that the physician contact the local poison control center for specific pediatric treatment.

DESCRIPTION

Cyclobenzaprine hydrochloride is a skeletal muscle relaxant which relieves muscle spasm of local origin without interfering with muscle function. The active ingredient in cyclobenzaprine hydrochloride extended-release capsules is cyclobenzaprine hydrochloride, USP. Cyclobenzaprine hydrochloride (HCl) is a white, crystalline tricyclic amine salt with the empirical formula C20H21N·HCl and a molecular weight of 311.9. It has a melting point of 217°C, and a pKa of 8.47 at 25°C. It is freely soluble in water and alcohol, sparingly soluble in isopropanol, and insoluble in hydrocarbon solvents. If aqueous solutions are made alkaline, the free base separates. Cyclobenzaprine HCl is designated chemically as 3-(5H-dibenzo[a,d] cyclohepten-5-ylidene)-N,N-dimethyl-1-propanamine hydrochloride, and has the following structural formula:

[Structural Formula]

Cyclobenzaprine hydrochloride extended-release capsules for oral administration are supplied in 15 and 30 mg strengths. Cyclobenzaprine hydrochloride extended-release capsules contain the following inactive ingredients: diethyl phthalate NF, ethylcellulose NF (Ethocel Standard 10 Premium), gelatin, Opadry® Clear YS-1-7006, sugar spheres NF (20-25 mesh), and titanium dioxide. Cyclobenzaprine hydrochloride extended-release 15 mg capsules also contain D&C yellow #10, FD&C green #3, and FD&C red #40. Cyclobenzaprine hydrochloride extended-release 30 mg capsules also contain FD&C blue #1, FD&C blue #2, FD&C red #40, and FD&C yellow #6.

CLINICAL PHARMACOLOGY

12.1 Mechanism of Action

Cyclobenzaprine relieves skeletal muscle spasm of local origin without interfering with muscle function. Cyclobenzaprine has not been shown to be effective in muscle spasm due to central nervous system disease. In animal models, cyclobenzaprine reduced or abolished skeletal muscle hyperactivity. Animal studies indicate that cyclobenzaprine does not act at the neuromuscular junction or directly on skeletal muscle. Such studies show that cyclobenzaprine acts primarily within the central nervous system at the brain stem as opposed to the spinal cord level, although an overlapping action on the latter may contribute to its overall skeletal muscle relaxant activity. Evidence suggests that the net effect of cyclobenzaprine is a reduction of tonic somatic motor activity, influencing both gamma (γ) and alpha (α) motor systems. Pharmacological studies in animals demonstrated a similarity between the effects of cyclobenzaprine and the structurally related tricyclic antidepressants, including reserpine antagonism, norepinephrine potentiation, potent peripheral and central anticholinergic effects, and sedation. Cyclobenzaprine caused slight to moderate increase in heart rate in animals.

12.3 Pharmacokinetics

Absorption

Following single-dose administration of cyclobenzaprine hydrochloride extended-release 15 mg and 30 mg capsules in healthy adult subjects (n=15), Cmax, AUC0-168h and AUC0-∞ increased in an approximately dose-proportional manner from 15 mg to 30 mg. The time to peak plasma cyclobenzaprine concentration (Tmax) was 7 to 8 hours for both doses of cyclobenzaprine hydrochloride extended-release capsules.

A food effect study conducted in healthy adult subjects (n=15) utilizing a single dose of cyclobenzaprine hydrochloride extended-release 30 mg capsules demonstrated a statistically significant increase in bioavailability when cyclobenzaprine hydrochloride extended-release 30 mg capsules were given with food relative to the fasted state. There was a 35% increase in peak plasma cyclobenzaprine concentration (Cmax) and a 20% increase in exposure (AUC0-168h and AUC0-∞) in the presence of food. No effect, however, was noted in Tmax or the shape of the mean plasma cyclobenzaprine concentration versus time profile. Cyclobenzaprine in plasma was first detectable in both the fed and fasted states at 1.5 hours.

When the contents of cyclobenzaprine hydrochloride extended-release capsules were administered by sprinkling on applesauce, it was found to be bioequivalent to the same dose when administered as an intact capsule.

In a multiple-dose study utilizing cyclobenzaprine hydrochloride extended-release 30 mg capsules administered once daily for 7 days in a group of healthy adult subjects (n=35), a 2.5-fold accumulation of plasma cyclobenzaprine levels was noted at steady-state.

Metabolism and Excretion

Cyclobenzaprine is extensively metabolized and is excreted primarily as glucuronides via the kidney. Cytochromes P-450 3A4, 1A2, and, to a lesser extent, 2D6, mediate N-demethylation, one of the oxidative pathways for cyclobenzaprine. Cyclobenzaprine has an elimination half-life of 32 hours (range 8-37 hours; n=18); plasma clearance is 0.7 L/min following single-dose administration of cyclobenzaprine hydrochloride extended-release capsules.

Special Populations

Elderly

Although there were no notable differences in Cmax or Tmax, cyclobenzaprine plasma AUC is increased by 40% and the plasma half-life of cyclobenzaprine is prolonged in elderly subjects greater than 65 years of age (50 hours) after dosing with cyclobenzaprine hydrochloride extended-release capsules compared to younger subjects 18 to 45 years of age (32 hours). Pharmacokinetic characteristics of cyclobenzaprine following multiple-dose administration of cyclobenzaprine hydrochloride extended-release capsules in the elderly were not evaluated.

Hepatic Impairment

In a pharmacokinetic study of immediate-release cyclobenzaprine in 16 subjects with hepatic impairment (15 mild, 1 moderate per Child-Pugh score), both AUC and Cmax were approximately double the values seen in the healthy control group. The pharmacokinetics of cyclobenzaprine in subjects with severe hepatic impairment is not known.

NONCLINICAL TOXICOLOGY

13.1 Carcinogenesis, Mutagenesis, Impairment of Fertility

Carcinogenesis

Long-term studies were conducted in CD-1 mice and Sprague-Dawley rats with oral cyclobenzaprine to evaluate its carcinogenic potential. In an 81-week carcinogenicity study, metastatic hemangiosarcoma was seen in 3 of 21 male mice at 10 mg/kg/day (approximately 2 times the maximum recommended human dose (MRHD) of 30 mg/day on a mg/m2 basis). In a 105-week carcinogenicity study, malignant astrocytoma was seen in 3 of 50 male rats at 10 mg/kg/day (approximately 3 times the MRHD on a mg/m2 basis). There were no tumor findings in female mice or rats.

Mutagenesis

Cyclobenzaprine HCl was not mutagenic or clastogenic in the following assays: an in vitro Ames bacterial mutation assay, in vitro Chinese hamster ovary (CHO) cell chromosomal aberration test, and in vivo mouse bone marrow micronucleus assay.

Impairment of Fertility

Cyclobenzaprine HCl, when administered 70 and 14 days prior to mating to male and female rats, respectively, had no effects on fertility or reproductive performance at oral doses up to 20 mg/kg/day (approximately 6.5 times the MRHD on a mg/m2 basis).

13.2 Animal Toxicology and/or Pharmacology

In a 67-week study with rats that received cyclobenzaprine at oral doses of 10, 20, or 40 mg/kg/day (3 to 15 times the MRHD on mg/m2 basis), there were findings in the liver consisting of midzonal vacuolation with lipidosis for males and midzonal and centrilobular hepatocytic enlargement for females. In addition, there were findings of centrilobular coagulative necrosis. In the higher dose groups, these microscopic changes were seen after 26 weeks and even earlier in rats that died prior to 26 weeks; at lower doses, these changes were not seen until after 26 weeks.

In a 26-week study with Cynomolgus monkeys that received cyclobenzaprine at oral of doses of 2.5, 5, 10, or 20 mg/kg/day, one monkey at 20 mg/kg/day (15 times the MRHD on mg/m2 basis) was euthanized in week 17. Morbidity for this animal was attributed to findings of chronic pancreatitis, cholecystitis, cholangitis, and focal liver necrosis.

CLINICAL STUDIES

Efficacy was assessed in two double-blind, parallel-group, active-controlled, placebo-controlled studies of identical design of cyclobenzaprine hydrochloride extended-release 15 mg and 30 mg capsules taken once daily, between 6:00 and 7:00 PM, cyclobenzaprine 10 mg three times a day, or placebo for 14 days in patients with muscle spasms associated with acute painful musculoskeletal conditions.

There were significant differences in the primary efficacy analysis, the patient’s rating of medication helpfulness, between the cyclobenzaprine hydrochloride extended-release capsules 15 mg group and the placebo group at Days 4 and 14 in one study and between the cyclobenzaprine hydrochloride extended-release capsules 30 mg group and the placebo group at Day 4 in the second study.

Table 2: Patients’ Rating of Medication Helpfulness - Study 1*

Day 4

Day 14

Number of Patients (%)

Number of Patients (%)

Placebo

(N = 64)

Cyclobenzaprine Hydrochloride Extended-Release Capsules 30 mg

(N = 64)

Placebo

(N = 64)

Cyclobenzaprine Hydrochloride Extended-Release Capsules 30 mg

(N = 64)

Excellent

1 (2%)

3 (5%)

12 (19%)

15 (23%)

Very Good

5 (8%)

13 (20%)

9 (14%)

19 (30%)

Good

15 (23%)

22 (34%)

10 (16%)

15 (23%)

Fair

24 (38%)

20 (31%)

16 (25%)

10 (16%)

Poor

10 (16%)

5 (8%)

9 (14%)

4 (6%)

Missing

9 (14%)

1 (2%)

8 (13%)

1 (2%)

* Percentages are rounded to the nearest whole percent.

Table 3: Patients’ Rating of Medication Helpfulness - Study 2*

Day 4

Day 14

Number of Patients (%)

Number of Patients (%)

Placebo

(N = 64)

Cyclobenzaprine Hydrochloride Extended-Release Capsules 15 mg

(N = 63)

Placebo

(N = 64)

Cyclobenzaprine Hydrochloride Extended-Release Capsules 15 mg

(N = 63)

Excellent

1 (2%)

2 (3%)

10 (16%)

13 (21%)

Very Good

10 (16%)

12 (19%)

12 (19%)

21 (33%)

Good

14 (22%)

21 (33%)

13 (20%)

9 (14%)

Fair

16 (25%)

17 (27%)

14 (22%)

10 (16%)

Poor

19 (30%)

6 (10%)

12 (19%)

5 (8%)

Missing

4 (6%)

5 (8%)

3 (5%)

5 (8%)

* Percentages are rounded to the nearest whole percent.

In addition, one of the two studies demonstrated significant differences between the cyclobenzaprine hydrochloride extended-release capsules 30 mg group and the placebo group in terms of patient-rated relief from local pain due to muscle spasm at Day 4 and Day 8, in patient-rated restriction of movement at Day 4 and Day 8, and in patient-rated global impression of change at Day 4, Day 8, and Day 14.

In both studies, there were no significant treatment differences between the cyclobenzaprine hydrochloride extended-release capsules treatment groups and the placebo group in physician's global assessment, patient-rated restriction in activities of daily living, or quality of nighttime sleep.

16.1 How Supplied

Cyclobenzaprine hydrochloride extended-release capsules are available in 15 and 30 mg strengths, packaged in bottles of 60 capsules. Cyclobenzaprine hydrochloride extended-release 15 mg capsules (NDC 0093-1920-06) are orange/orange and are embossed in blue ink with “15 mg” on the body, and Cephalon “C” logo, “Cephalon”, and a dashed band on the cap. Cyclobenzaprine hydrochloride extended-release 30 mg capsules (NDC 0093-1921-06) are blue/red and are embossed in white ink with “30 mg” on the body, and Cephalon “C” logo, “Cephalon”, and a dashed band on the cap.

16.2 Storage and Handling

Dispense in a tight, light-resistant container as defined in the USP/NF.

Store at 25°C (77°F); excursions permitted to 15 - 30°C (59 - 86°F) [see USP Controlled Room Temperature].

See FDA-approved patient labeling (Patient Information).

Instruct patients to swallow cyclobenzaprine hydrochloride extended-release capsules intact or to sprinkle capsule contents on a tablespoon of applesauce and swallow immediately without chewing.
Advise patients to stop taking cyclobenzaprine hydrochloride extended-release capsules and to notify their physician right away if they experience symptoms of an allergic reaction, such as difficulty breathing, hives, swelling of face or tongue, or itching.
Advise patients that cyclobenzaprine hydrochloride extended-release capsules should not be taken with MAO inhibitors or within 14 days after their discontinuation.
Caution patients about the risk of serotonin syndrome with concomitant use of cyclobenzaprine hydrochloride extended-release capsules and other drugs, such as SSRIs, SNRIs, TCAs, tramadol, bupropion, meperidine, verapamil, or MAO inhibitors. Advise patients of the signs and symptoms of serotonin syndrome [SEE WARNINGS AND PRECAUTIONS (5.1)] and instruct patients to seek medical care immediately if they experience these symptoms.
Advise patients to stop taking cyclobenzaprine hydrochloride extended-release capsules and to notify their physician right away if they experience arrhythmias or tachycardia.
Advise patients that cyclobenzaprine hydrochloride extended-release capsules may enhance the impairment effects of alcohol. These effects may also be seen if cyclobenzaprine hydrochloride extended-release capsules are taken with other CNS depressants.
Caution patients about operating an automobile or other hazardous machinery until it is reasonably certain that cyclobenzaprine hydrochloride extended-release capsules therapy will not adversely affect their ability to engage in such activities.
Advise patients to take cyclobenzaprine hydrochloride extended-release capsules at approximately the same time each day.

Distributed By:
Teva Pharmaceuticals USA, Inc.
Parsippany, NJ 07054

Manufactured By:
Adare Pharmaceuticals, Inc.
Vandalia, OH 45377

Revised May 2020

CHERC-004

© 2020 Teva Pharmaceuticals USA, Inc.
All rights reserved.

INSTRUCTIONS FOR USE

Cyclobenzaprine Hydrochloride Extended-Release Capsules

Read this Instructions for Use before you prepare your first dose of cyclobenzaprine hydrochloride extended-release capsules mixed with applesauce using the capsule sprinkle method, each time you get a refill, and as needed. There may be new information. Ask your healthcare provider or pharmacist if you have any questions about how to mix or give a dose of cyclobenzaprine hydrochloride extended-release capsules using the capsule sprinkle method.

Important Information:

Do not chew cyclobenzaprine hydrochloride extended-release capsules or the granules that are in the capsules.
The capsule sprinkle method for mixing the contents of cyclobenzaprine hydrochloride extended-release capsules with applesauce may be used for adults who cannot swallow capsules. Do not use any other food in the place of applesauce.

Preparing a dose of cyclobenzaprine hydrochloride extended-release capsules using the capsule sprinkle method.

Before you prepare a dose of cyclobenzaprine hydrochloride extended-release capsules mixed with applesauce using the capsule sprinkle method, gather the following supplies:

paper towels
tablespoon
applesauce
cup of water

Step 1: Choose a clean, flat work surface. Place a clean paper towel on the work surface. Then place the other supplies on the paper towel.
Step 2: Wash and dry your hands well.
Step 3: Check the dose that was prescribed by your healthcare provider. Take out the number of cyclobenzaprine hydrochloride extended-release capsules needed to prepare your dose. Place them on the paper towel.
Step 4: Place enough applesauce to fill your tablespoon. Set the tablespoon down on the paper towel. [image]
Step 5: Hold the cyclobenzaprine hydrochloride extended-release capsule in an upright position (vertical) directly over the tablespoon. Hold each end of the cyclobenzaprine hydrochloride extended-release capsule between your thumbs and index (pointer) fingers. [image]
Step 6: Carefully twist both ends of the cyclobenzaprine hydrochloride extended-release capsule in opposite directions to open it. Be careful not to spill the capsule contents. [image]

Step 7: Sprinkle the contents of the cyclobenzaprine hydrochloride extended-release capsule onto the applesauce.

Check the capsule shells to make sure they are empty.
Throw away the empty capsule shells.

If the total prescribed dose is more than 1 capsule, repeat Steps 5 through 7 for each capsule. Do not add more applesauce. Then follow the rest of the steps below. [image]
Step 8: Pick up the tablespoon and swallow the cyclobenzaprine hydrochloride extended-release capsule contents and applesauce mixture right away. Do not chew the cyclobenzaprine hydrochloride extended-release capsule contents and applesauce mixture. [image]
Step 9: Rinse your mouth with a sip of water and swallow to make sure that all of the cyclobenzaprine hydrochloride extended-release capsule granules have been swallowed. [image]
Step 10: Throw away any unused cyclobenzaprine hydrochloride extended-release capsule content and applesauce mixture. Do not keep any cyclobenzaprine hydrochloride extended-release capsule content and applesauce mixture for future use.

How should I store cyclobenzaprine hydrochloride extended-release capsules?

Store cyclobenzaprine hydrochloride extended-release capsules at room temperature between 68°F to 77°F (20°C to 25°C).

Keep cyclobenzaprine hydrochloride extended-release capsules and all medicines out of the reach of children.

This Instructions for Use has been approved by the U.S. Food and Drug Administration.

CHERCIFU-001

Issued: May 2019